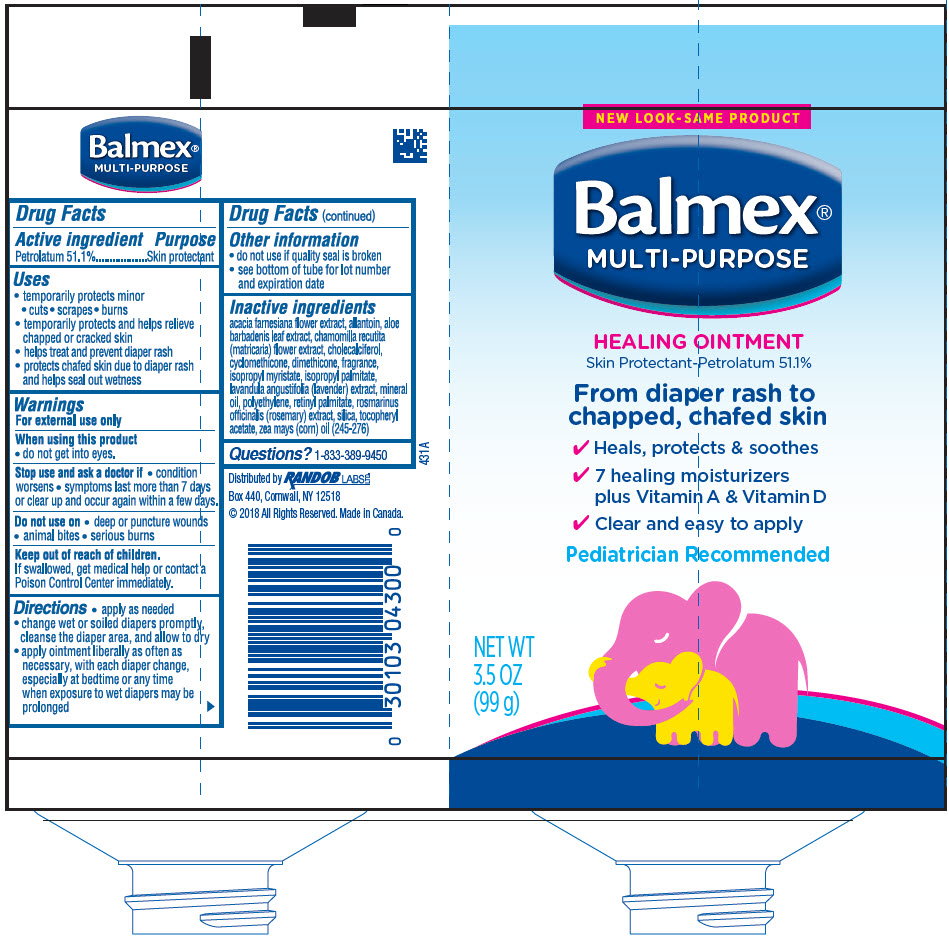 DRUG LABEL: BALMEX MULTI-PURPOSE
NDC: 52412-450 | Form: OINTMENT
Manufacturer: Randob Labs,Ltd.
Category: otc | Type: HUMAN OTC DRUG LABEL
Date: 20181113

ACTIVE INGREDIENTS: Petrolatum 511 mg/1 g
INACTIVE INGREDIENTS: Vachellia Farnesiana Flower; Allantoin; Aloe Vera Leaf; Chamomile; Cholecalciferol; Cyclomethicone 5; Cyclomethicone 6; Dimethicone 200; Isopropyl Myristate; Isopropyl Palmitate; Lavandula Angustifolia Subsp. Angustifolia Flowering Top; Mineral Oil; High Density Polyethylene; Vitamin A Palmitate; Rosemary; Silicon Dioxide; .alpha.-tocopherol Acetate, Dl-; Corn Oil

BALMEX® MULTI-PURPOSE

Drug Facts

ACTIVE INGREDIENT

Active ingredients | Purpose
Petrolatum 51.1% | Skin protectant

Uses

- temporarily protects minor
  - cuts
  - scrapes
  - burns
- temporarily protects and helps relieve chapped or cracked skin
- helps treat and prevent diaper rash
- protects chafed skin due to diaper rash and helps seal out wetness

Warnings

For external use only

When using this product

- do not get into eyes.

Stop use and ask a doctor if

- condition worsens
- symptoms last more than 7 days or clear up and occur again within a few days.

Do not use on

- deep or puncture wounds
- animal bites
- serious burns

Keep out of reach of children. If swallowed, get medical help or contact a Poison Control Center immediately.

Directions

- apply as needed
- change wet or soiled diapers promptly, cleanse the diaper area, and allow to dry
- apply ointment liberally as often as necessary, with each diaper change, especially at bedtime or any time when exposure to wet diapers may be prolonged

Other information

- do not use if quality seal is broken
- see bottom of tube for lot number and expiration date

Inactive ingredients

acacia farnesiana flower extract, allantoin, aloe barbadenis leaf extract, chamomilla recutita (matricaria) flower extract, cholecalciferol, cyclomethicone, dimethicone, fragrance, isopropyl myristate, isopropyl palmitate, lavandula angustifolia (lavender) extract, mineral oil, polyethylene, retinyl palmitate, rosmarinus officinalis (rosemary) extract, silica, tocopheryl acetate, zea mays (corn) oil (245-276)

Questions?

1-833-389-9450

Distributed by RANDOB LABS LTD.
Box 440, Cornwall, NY 12518

PRINCIPAL DISPLAY PANEL - 99 g Tube Label

NEW LOOK-SAME PRODUCT

Balmex®
MULTI-PURPOSE

HEALING OINTMENT
Skin Protectant-Petrolatum 51.1%

From diaper rash to
chapped, chafed skin

✔ Heals, protects & soothes
✔ 7 healing moisturizers
  plus Vitamin A & Vitamin D
✔ Clear and easy to apply

Pediatrician Recommended

NET WT
3.5 OZ
(99 g)